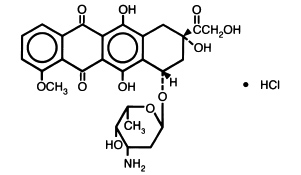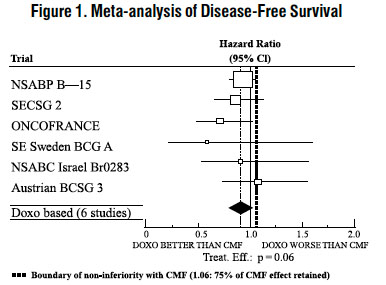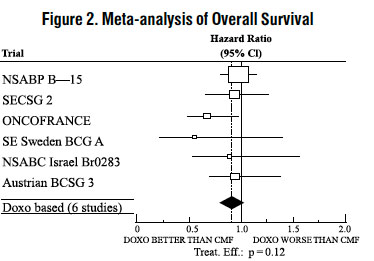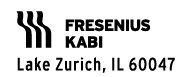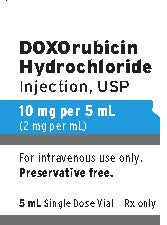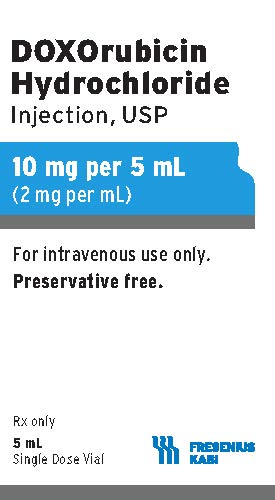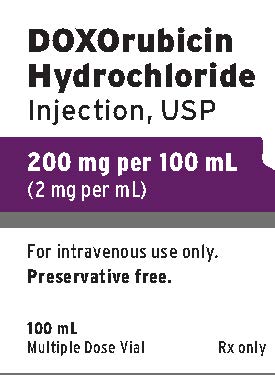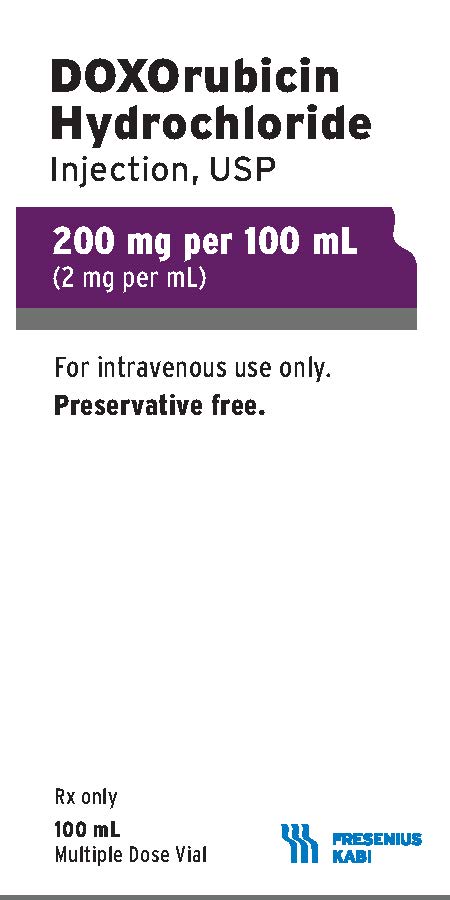 DRUG LABEL: Doxorubicin Hydrochloride

NDC: 63323-883 | Form: INJECTION, SOLUTION
Manufacturer: Fresenius Kabi USA, LLC
Category: prescription | Type: HUMAN PRESCRIPTION DRUG LABEL
Date: 20241014

ACTIVE INGREDIENTS: DOXORUBICIN HYDROCHLORIDE 2 mg/1 mL
INACTIVE INGREDIENTS: SODIUM CHLORIDE 9 mg/1 mL; HYDROCHLORIC ACID; SODIUM HYDROXIDE

Doxorubicin Hydrochloride Injection USP

WARNING

1. Severe local tissue necrosis will occur if there is extravasation during administration (see DOSAGE AND ADMINISTRATION). Doxorubicin must not be given by the intramuscular or subcutaneous route.
2. Myocardial toxicity manifested in its most severe form by potentially fatal congestive heart failure (CHF) may occur either during therapy or months to years after termination of therapy. The probability of developing impaired myocardial function based on a combined index of signs, symptoms and decline in left ventricular ejection fraction (LVEF) is estimated to be 1 to 2% at a total cumulative dose of 300 mg/m^2 of doxorubicin, 3 to 5% at a dose of 400 mg/m^2, 5 to 8% at 450 mg/m^2 and 6 to 20% at 500 mg/m^2. The risk of developing CHF increases rapidly with increasing total cumulative doses of doxorubicin in excess of 400 mg/m^2. Risk factors (active or dormant cardiovascular disease, prior or concomitant radiotherapy to the mediastinal/pericardial area, previous therapy with other anthracyclines or anthracenediones, concomitant use of other cardiotoxic drugs) may increase the risk of cardiac toxicity. Cardiac toxicity with doxorubicin may occur at lower cumulative doses whether or not cardiac risk factors are present. Pediatric patients are at increased risk for developing delayed cardiotoxicity.
3. Secondary acute myelogenous leukemia (AML) or myelodysplastic syndrome (MDS) has been reported in patients treated with anthracyclines, including doxorubicin (see ADVERSE REACTIONS). The occurrence of refractory secondary AML or MDS is more common when anthracyclines are given in combination with DNA-damaging anti-neoplastic agents or radiotherapy, when patients have been heavily pretreated with cytotoxic drugs, or when doses of anthracyclines have been escalated. The rate of developing secondary AML or MDS has been estimated in an analysis of 8,563 patients with early breast cancer treated in 6 studies conducted by the National Surgical Adjuvant Breast and Bowel Project (NSABP), including NSABP B-15. Patients in these studies received standard doses of doxorubicin and standard or escalated doses of cyclophosphamide (AC) adjuvant chemotherapy and were followed for 61,810 patient years. Among 4,483 such patients who received conventional doses of AC, 11 cases of AML or MDS were identified, for an incidence of 0.32 cases per 1,000 patient years (95% Cl, 0.16 to 0.57) and a cumulative incidence at 5 years of 0.21% (95% Cl, 0.11 to 0.41%). In another analysis of 1,474 patients with breast cancer who received adjuvant treatment with doxorubicin-containing regimens in clinical trials conducted at University of Texas M.D. Anderson Cancer Center, the incidence was estimated at 1.5% at 10 years. In both experiences, patients who received regimens with higher cyclophosphamide dosages, who received radiotherapy, or who were aged 50 or older had an increased risk of secondary AML or MDS. Pediatric patients are also at risk of developing secondary AML.
4. Dosage should be reduced in patients with impaired hepatic function.
5. Severe myelosuppression may occur.
6. Doxorubicin should be administered only under the supervision of a physician who is experienced in the use of cancer chemotherapeutic agents.

DESCRIPTION:

Doxorubicin is a cytotoxic anthracycline antibiotic isolated from cultures of Streptomyces peucetius var . caesius. Doxorubicin consists of a naphthacenequinone nucleus linked through a glycosidic bond at ring atom 7 to an amino sugar, daunosamine. Chemically, doxorubicin hydrochloride is: 5,12-Naphthacenedione, 10-[(3-amino-2,3,6-trideoxy-α-L- lyxo-hexopyranosyl)oxy]-7,8,9,10-tetrahydro-6,8,11-trihydroxy-8-(hydroxylacetyl)-1-methoxy-, hydrochloride (8 S- cis)-. (8 S, 10 S)-10-[(3-Amino-2,3,6-trideoxy-α-L- lyxo-hexopyranosyl)-oxy]-8-glycoloyl-7,8,9,10-tetrahydro-6,8,11-trihydroxy-1-methoxy-5,12-naphthacenedione hydrochloride [ 25316-40-9].

The structural formula is as follows:

C27H29NO11• HCl M.W.579.99
Doxorubicin binds to nucleic acids, presumably by specific intercalation of the planar anthracycline nucleus with the DNA double helix. The anthracycline ring is lipophilic, but the saturated end of the ring system contains abundant hydroxyl groups adjacent to the amino sugar, producing a hydrophilic center. The molecule is amphoteric, containing acidic functions in the ring phenolic groups and a basic function in the sugar amino group. It binds to cell membranes as well as plasma proteins.

Doxorubicin Hydrochloride Injection, USP is a sterile, isotonic, preservative-free solution for intravenous use. It is available in 5 mL (10 mg), 10 mL (20 mg) and 25 mL (50 mg) single dose vials and 100 mL (200 mg) multiple dose vials.

Each mL contains: Doxorubicin hydrochloride 2 mg; sodium chloride 9 mg for Isotonicity: Water for Injection q.s. Hydrochloric acid and/or sodium hydroxide may have been added for pH adjustment (2.5 to 4.5).

CLINICAL PHARMACOLOGY:

The cytotoxic effect of doxorubicin on malignant cells and its toxic effects on various organs are thought to be related to nucleotide base intercalation and cell membrane lipid binding activities of doxorubicin. Intercalation inhibits nucleotide replication and action of DNA and RNA polymerases. The interaction of doxorubicin with topoisomerase II to form DNA-cleavable complexes appears to be an important mechanism of doxorubicin cytocidal activity.

Doxorubicin cellular membrane binding may affect a variety of cellular functions. Enzymatic electron reduction of doxorubicin by a variety of oxidases, reductases and dehydrogenases generates highly reactive species including the hydroxyl free radical OH•. Free radical formation has been implicated in doxorubicin cardiotoxicity by means of Cu (II) and Fe (III) reduction at the cellular level.

Cells treated with doxorubicin have been shown to manifest the characteristic morphologic changes associated with apoptosis or programmed cell death. Doxorubicin-induced apoptosis may be an integral component of the cellular mechanism of action relating to therapeutic effects, toxicities, or both.

Animal studies have shown activity in a spectrum of experimental tumors, immunosuppression, carcinogenic properties in rodents, induction of a variety of toxic effects, including delayed and progressive cardiac toxicity, myelosuppression in all species and atrophy to testes in rats and dogs.

Pharmacokinetics

Pharmacokinetic studies, determined in patients with various types of tumors undergoing either single or multi-agent therapy have shown that doxorubicin follows a multiphasic disposition after intravenous injection. In four patients, doxorubicin has demonstrated dose-independent pharmacokinetics in the dose range of 30 to 70 mg/m^2.

Distribution

The initial distribution half-life of approximately 5 minutes suggests rapid tissue uptake of doxorubicin, while its slow elimination from tissues is reflected by a terminal half-life of 20 to 48 hours. Steady-state distribution volume ranges from 809 to 1,214 L/m^2 and is indicative of extensive drug uptake into tissues. Binding of doxorubicin and its major metabolite, doxorubicinol, to plasma proteins is about 74 to 76% and is independent of plasma concentration of doxorubicin up to 1.1 mcg/mL.

Doxorubicin was excreted in the milk of one lactating patient, with peak milk concentration at 24 hours after treatment being approximately 4.4-fold greater than the corresponding plasma concentration. Doxorubicin was detectable in the milk up to 72 hours after therapy with 70 mg/m^2 of doxorubicin given as a 15-minute intravenous infusion and 100 mg/m^2 of cisplatin as a 26-hour intravenous infusion. The peak concentration of doxorubicinol in milk at 24 hours was 0.11 mcg/mL and AUC up to 24 hours was 9 mcg•h/mL while the AUC for doxorubicin was 5.4 mcg•h/mL.

Doxorubicin does not cross the blood brain barrier.

Metabolism

Enzymatic reduction at the 7 position and cleavage of the daunosamine sugar yields aglycones which are accompanied by free radical formation, the local production of which may contribute to the cardiotoxic activity of doxorubicin. Disposition of doxorubicinol (DOX-OL) in patients is formation rate limited, with the terminal half-life of DOX-OL being similar to doxorubicin. The relative exposure of DOX-OL, i.e., the ratio between the AUC of DOX-OL and the AUC of doxorubicin, compared to doxorubicin ranges between 0.4 and 0.6.

Excretion

Plasma clearance is in the range 324 to 809 mL/min/m^2 and is predominately by metabolism and biliary excretion. Approximately 40% of the dose appears in the bile in 5 days, while only 5 to 12% of the drug and its metabolites appear in the urine during the same time period. In urine, < 3% of the dose was recovered as DOX-OL over 7 days.

Systemic clearance of doxorubicin is significantly reduced in obese women with ideal body weight greater than 130%. There was a significant reduction in clearance without any change in volume of distribution in obese patients when compared with normal patients with less than 115% ideal body weight.

Pharmacokinetics in Special Populations

Pediatric

Following administration of 10 to 75 mg/m^2 doses of doxorubicin to 60 children and adolescents ranging from 2 months to 20 years of age, doxorubicin clearance averaged 1,443 ± 114 mL/min/m^2. Further analysis demonstrated that clearance in 52 children greater than 2 years of age (1,540 mL/min/m^2) was increased compared with adults. However, clearance in infants younger than 2 years of age (813 mL/min/m^2) was decreased compared with older children and approached the range of clearance values determined in adults.

Geriatric

While the pharmacokinetics of elderly subjects (≥65 years of age) have been evaluated, no dosage adjustment is recommended based on age (see PRECAUTIONS, Geriatric Use).

Gender

A published clinical study involving 6 men and 21 women with no prior anthracycline therapy reported a significantly higher median doxorubicin clearance in the men compared to the women (1,088 mL/min/m^2 versus 433 mL/min/m^2). However, the terminal half-life of doxorubicin was longer in men compared to the women (54 versus 35 hours).

Race

The influence of race on the pharmacokinetics of doxorubicin has not been evaluated.

Hepatic Impairment

The clearance of doxorubicin and doxorubicinol was reduced in patients with impaired hepatic function (see DOSAGE AND ADMINISTRATION).

Renal Impairment

The influence of renal function on the pharmacokinetics of doxorubicin has not been evaluated.

CLINICAL STUDIES:

The effectiveness of doxorubicin-containing regimens in the adjuvant therapy of early breast cancer has primarily been established based on data collected in a meta-analysis published in 1998 by the Early Breast Cancer Trialists Collaborative Group (EBCTCG). The EBCTCG obtains primary data on all relevant studies, both published and unpublished, for early stage breast cancer and regularly updates these analyses. The principal endpoints for the adjuvant chemotherapy trials were disease-free survival (DFS) and overall survival (OS). The meta-analyses allowed comparisons of cyclophosphamide, methotrexate, and 5-fluorouracil (CMF) to no chemotherapy (19 trials including 7,523 patients) and comparisons of doxorubicin-containing regimens with CMF as an active control (6 trials including 3,510 patients). The pooled estimates of DFS and OS from these trials were used to calculate the effect of CMF relative to no therapy. The hazard ratio for DFS for CMF compared to no chemotherapy was 0.76 (95% Cl, 0.71 to 0.82) and for OS was 0.86 (95% Cl, 0.8 to 0.93). Based on a conservative estimate of CMF effect (lower 2-sided 95% confidence limit of hazard ratio) and 75% retention of CMF effect on DFS, it was determined that the doxorubicin-containing regimens would be considered as non-inferior to CMF if the upper 2-sided 95% confidence limit of the hazard ratio was less than 1.06, i.e., not more than 6% worse than CMF. A similar calculation for OS would require a non-inferiority margin of 1.02.

Six randomized trials in the EBCTCG meta-analysis compared doxorubicin-containing regimens to CMF. A total of 3,510 women with early breast cancer involving axillary lymph nodes were evaluated; approximately 70% were premenopausal and 30% were postmenopausal. At the time of the meta-analysis, 1,745 first recurrences and 1,348 deaths had occurred. Analyses demonstrated that doxorubicin-containing regimens retained at least 75% of the historical CMF adjuvant effect on DFS and are effective. The hazard ratio for DFS (dox:CMF) was 0.91 (95% Cl, 0.82 to 1.01) and for OS was 0.91 (95% Cl, 0.81 to 1.03). Results of these analyses for both DFS and OS are provided in Table 1 and Figures 1 and 2.

Table 1. Summary of Randomized Trials Comparing Doxorubicin-Containing Regimens Versus CMF in EBCTCG Meta-Analysis

Study (starting year) | Regimens | No. of Cycles | No. of Patients | Doxorubicin-Containing Regimens vs CMF HR (95% CI)
Study (starting year) | Regimens | No. of Cycles | No. of Patients | DFS | OS
NSABP B-15 (1984) | AC | 4 | 1,562* | 0.93 (0.82 to 1.06) | 0.97 (0.83 to 1.12)
NSABP B-15 (1984) | CMF | 6 | 776 | 0.93 (0.82 to 1.06) | 0.97 (0.83 to 1.12)
SECSG 2 (1976) | FAC | 6 | 260 | 0.86 (0.66 to 1.13) | 0.93 (0.69 to 1.26)
SECSG 2 (1976) | CMF | 6 | 268 | 0.86 (0.66 to 1.13) | 0.93 (0.69 to 1.26)
ONCOFRANCE (1978) | FACV | 12 | 138 | 0.71 (0.49 to 1.03) | 0.65 (0.44 to 0.96)
ONCOFRANCE (1978) | CMF | 12 | 113 | 0.71 (0.49 to 1.03) | 0.65 (0.44 to 0.96)
SE Sweden BCG A (1980) | AC | 6 | 21 | 0.59 (0.22 to 1.61) | 0.53 (0.21 to 1.37)
SE Sweden BCG A (1980) | CMF | 6 | 22 | 0.59 (0.22 to 1.61) | 0.53 (0.21 to 1.37)
NSABC Israel Br0283 (1983) | AVbCMF† CMF | 4 6 6 | 55 50 | 0.91 (0.53 to 1.57) | 0.88 (0.47 to 1.63)
Austrian BCSG 3 (1984) | CMFVA | 6 | 121 | 1.07 (0.73 to 1.55) | 0.93 (0.64 to 1.35)
Austrian BCSG 3 (1984) | CMF | 8 | 124 | 1.07 (0.73 to 1.55) | 0.93 (0.64 to 1.35)
Combined Studies | Doxorubicin-Containing Regimens |  | 2,157 | 0.91 (0.82 to 1.01) | 0.91 (0.81 to 1.03)
Combined Studies | CMF |  | 1,353 | 0.91 (0.82 to 1.01) | 0.91 (0.81 to 1.03)

Abbreviations: DFS = disease free survival; OS = overall survival; AC = doxorubicin, cyclophosphamide; AVbCMF = doxorubicin, vinblastine, cyclophosphamide, methotrexate, 5-fluorouracil; CMF = cyclophosphamide, methotrexate, 5-fluorouracil; CMFVA = cyclophosphamide, methotrexate, 5-fluorouracil, vincristine, doxorubicin; FAC = 5-fluorouracil, doxorubicin, cyclophosphamide; FACV = 5-fluorouracil, doxorubicin, cyclophosphamide, vincristine; HR = hazard ratio; CI = confidence interval

_________________________________________________________________________________________________________________________

* Includes pooled data from patients who received either AC alone for 4 cycles, or who were treated with AC for 4 cycles followed by 3 cycles of CMF.

† Patients received alternating cycles of AVb and CMF.

With respect to DFS, 2 of 6 studies (NSABP B-15 and ONCOFRANCE) met the non-inferiority standard individually and with respect to OS, 1 study met the non-inferiority margin individually (ONCOFRANCE). The largest of the 6 studies in the EBCTCG meta-analysis, a randomized, open-label, multicenter trial (NSABP B-15) was conducted in approximately 2,300 women (80% premenopausal; 20% postmenopausal) with early breast cancer involving axillary lymph nodes. In this trial, 6 cycles of conventional CMF was compared to 4 cycles of doxorubicin and cyclophosphamide (AC) and 4 cycles of AC followed by 3 cycles of CMF. No statistically significant differences in terms of DFS or OS were observed (see Table 1).

INDICATIONS AND USAGE:

Doxorubicin Hydrochloride Injection, USP has been used successfully to produce regression in disseminated neoplastic conditions such as acute lymphoblastic leukemia, acute myeloblastic leukemia, Wilms' tumor, neuroblastoma, soft tissue and bone sarcomas, breast carcinoma, ovarian carcinoma, transitional cell bladder carcinoma, thyroid carcinoma, gastric carcinoma, Hodgkin's disease, malignant lymphoma and bronchogenic carcinoma in which the small cell histologic type is the most responsive compared to other cell types.

Doxorubicin is also indicated for use as a component of adjuvant therapy in women with evidence of axillary lymph node involvement following resection of primary breast cancer.

CONTRAINDICATIONS:

Patients should not be treated with doxorubicin if they have any of the following conditions: baseline neutrophil count <1,500 cells/mm^3; severe hepatic impairment; recent myocardial infarction; severe myocardial insufficiency; severe arrhythmias; previous treatment with complete cumulative doses of doxorubicin, daunorubicin, idarubicin, and/or other anthracyclines and anthracenediones; or hypersensitivity to doxorubicin, any of its excipients, or other anthracyclines or anthracenediones (see WARNINGS and DOSAGE AND ADMINISTRATION).

WARNINGS:

General

Doxorubicin should be administered only under the supervision of qualified physicians experienced in the use of cytotoxic therapy. Patients should recover from acute toxicities of prior cytotoxic treatment (such as stomatitis, neutropenia, thrombocytopenia, and generalized infections) before beginning treatment with doxorubicin. Also, initial treatment with doxorubicin should be preceded by a careful baseline assessment of blood counts; serum levels of total bilirubin, AST, and creatinine; and cardiac function as measured by left ventricular ejection function (LVEF). Patients should be carefully monitored during treatment for possible clinical complications due to myelosuppression. Supportive care may be necessary for the treatment of severe neutropenia and severe infectious complications. Monitoring for potential cardiotoxicity is also important, especially with greater cumulative exposure to doxorubicin. Doxorubicin may potentiate the toxicity of other anticancer therapies (see PRECAUTIONS, Drug Interactions).

Cardiac Function

Cardiotoxicity is a known risk of anthracycline treatment. Anthracycline-induced cardiotoxicity may be manifested by early (or acute) or late (delayed) events. Early cardiotoxicity of doxorubicin consists mainly of sinus tachycardia and/or electrocardiogram (ECG) abnormalities such as non-specific ST-T wave changes. Tachyarrhythmias, including premature ventricular contractions and ventricular tachycardia, bradycardia, as well as atrioventricular and bundle-branch block have also been reported. These effects do not usually predict subsequent development of delayed cardiotoxicity, are rarely of clinical importance, and are generally not considered an indication for the suspension of doxorubicin treatment.

Delayed cardiotoxicity usually develops late in the course of therapy with doxorubicin or within 2 to 3 months after treatment termination, but later events, several months to years after completion of treatment, have also been reported. Delayed cardiomyopathy is manifested by a reduction in LVEF and/or signs and symptoms of congestive heart failure (CHF) such as tachycardia, dyspnea, pulmonary edema, dependent edema, cardiomegaly and hepatomegaly, oliguria, ascites, pleural effusion, and gallop rhythm. Subacute effects such as pericarditis/myocarditis have also been reported. Life-threatening CHF is the most severe form of anthracycline-induced cardiomyopathy and represents the cumulative dose-limiting toxicity of the drug.

The probability of developing impaired myocardial function, based on a combined index of signs, symptoms and decline in left ventricular ejection fraction (LVEF) is estimated to be 1 to 2% at a total cumulative dose of 300 mg/m^2 of doxorubicin, 3 to 5% at a dose of 400 mg/m^2, 5 to 8% at a dose of 450 mg/m^2 and 6 to 20% at a dose of 500 mg/m^2 given in a schedule of a bolus injection once every 3 weeks. In a retrospective review, the probability of developing congestive heart failure was reported to be 5/168 (3%) at a cumulative dose of 430 mg/m^2 of doxorubicin, 8/110 (7%) at 575 mg/m^2, and 3/14 (21%) at 728 mg/m^2. In a prospective study of doxorubicin in combination with cyclophosphamide, fluorouracil and/or vincristine in patients with breast cancer or small cell lung cancer, the probability of CHF at various cumulative doses of doxorubicin was 1.5% at 300 mg/m^2, 4.9% at 400 mg/m^2, 7.7% at 450 mg/m^2 and 20.5% at 500 mg/m^2. The risk of developing CHF increases rapidly with increasing total cumulative doses of doxorubicin in excess of 400 mg/m^2.

Cardiotoxicity may occur at lower doses in patients with prior mediastinal/pericardial irradiation, concomitant use of other cardiotoxic drugs, doxorubicin exposure at an early age, and advanced age. Data also suggest that pre-existing heart disease is a co-factor for increased risk of doxorubicin cardiotoxicity. In such cases, cardiac toxicity may occur at doses lower than the recommended cumulative dose of doxorubicin. Studies have suggested that concomitant administration of doxorubicin and calcium channel entry blockers or cardiotoxic drugs, especially those with long half-lives, e.g. trastuzumab, may increase the risk of doxorubicin cardiotoxicity (see PRECAUTIONS, General, DOSAGE AND ADMINISTRATION). The total dose of doxorubicin administered to the individual patient should also take into account previous or concomitant therapy with related compounds such as daunorubicin, idarubicin and mitoxantrone. Although not formally tested, it is probable that the toxicity of doxorubicin and other anthracyclines or anthracenediones is additive. Cardiomyopathy and/or congestive heart failure may be encountered several months or years after discontinuation of doxorubicin therapy.

The risk of acute manifestations of doxorubicin cardiotoxicity in pediatric patients may be as much or lower than in adults. Pediatric patients appear to be at particular risk for developing delayed cardiac toxicity in that doxorubicin-induced cardiomyopathy impairs myocardial growth as pediatric patients mature, subsequently leading to possible development of congestive heart failure during early adulthood. As many as 40% of pediatric patients may have subclinical cardiac dysfunction and 5 to 10% of pediatric patients may develop congestive heart failure on long term follow-up. This late cardiac toxicity may be related to the dose of doxorubicin. The longer the length of follow-up, the greater the increase in the detection rate. Treatment of doxorubicin-induced congestive heart failure includes the use of digitalis, diuretics, after load reducers such as angiotensin I converting enzyme (ACE) inhibitors, low salt diet, and bed rest. Such intervention may relieve symptoms and improve the functional status of the patient.

Monitoring Cardiac Function

The risk of serious cardiac impairment may be decreased through regular monitoring of LVEF during the course of treatment with prompt discontinuation of doxorubicin at the first sign of impaired function. The preferred method for assessment of cardiac function is evaluation of LVEF measured by multi-gated radionuclide angiography (MUGA) or echocardiography (ECHO). An ECG may also be done. A baseline cardiac evaluation with a MUGA scan or an ECHO is recommended, especially in patients with risk factors for increased cardiac toxicity. Repeated MUGA or ECHO determinations of LVEF should be performed, particularly with higher, cumulative anthracycline doses. The technique used for assessment should be consistent through follow-up. In patients with risk factors, particularly prior anthracycline or anthracenedione use, the monitoring of cardiac function must be particularly strict and the risk-benefit of continuing treatment with doxorubicin in patients with impaired cardiac function must be carefully evaluated.

Endomyocardial biopsy is recognized as the most sensitive diagnostic tool to detect anthracycline-induced cardiomyopathy; however, this invasive examination is not practically performed on a routine basis. ECG changes such as dysrhythmias, a reduction of the QRS voltage, or a prolongation beyond normal limits of the systolic time interval may be indicative of anthracycline-induced cardiomyopathy, but ECG is not a sensitive or specific method for following anthracycline-related cardiotoxicity.

Pediatric patients are at increased risk for developing delayed cardiotoxicity following doxorubicin administration and therefore a follow-up cardiac evaluation is recommended periodically to monitor for this delayed cardiotoxicity.

In adults, a 10% decline in LVEF to below the lower limit of normal or an absolute LVEF of 45%, or a 20% decline in LVEF at any level is indicative of deterioration in cardiac function. In pediatric patients, deterioration in cardiac function during or after the completion of therapy with doxorubicin is indicated by a drop in fractional shortening (FS) by an absolute value of ≥ 10 percentile units or below 29%, and a decline in LVEF of 10 percentile units or an LVEF below 55%. In general, if test results indicate deterioration in cardiac function associated with doxorubicin, the benefit of continued therapy should be carefully evaluated against the risk of producing irreversible cardiac damage. Acute life-threatening arrhythmias have been reported to occur during or within a few hours after doxorubicin administration.

Hematologic Toxicity

As with other cytotoxic agents, doxorubicin may produce myelosuppression. Myelosuppression requires careful monitoring. Total and differential WBC, red blood cell (RBC), and platelet counts should be assessed before and during each cycle of therapy with doxorubicin. A dose-dependent, reversible leukopenia and/or granulocytopenia (neutropenia) are the predominant manifestations of doxorubicin hematologic toxicity and is the most common acute dose-limiting toxicities of this drug. With the recommended dose schedule, leukopenia is usually transient, reaching its nadir 10 to 14 days after treatment with recovery usually occurring by the 21st day. Thrombocytopenia and anemia may also occur. Clinical consequences of severe myelosuppression include fever, infections, sepsis/septicemia, septic shock, hemorrhage, tissue hypoxia, or death.

Secondary Leukemia

The occurrence of secondary AML or MDS has been reported most commonly in patients treated with chemotherapy regimens containing anthracyclines (including doxorubicin) and DNA-damaging antineoplastic agents, in combination with radiotherapy, when patients have been heavily pretreated with cytotoxic drugs, or when doses of anthracyclines have been escalated. Such cases generally have a 1 to 3 year latency period. The rate of developing secondary AML or MDS has been estimated in an analysis of 8,563 patients with early breast cancer treated in 6 studies conducted by the National Surgical Adjuvant Breast and Bowel Project (NSABP), including NSABP B-15. Patients in these studies received standard doses of doxorubicin and standard or escalated doses of cyclophosphamide (AC) adjuvant chemotherapy and were followed for 61,810 patient years. Among 4,483 such patients who received conventional doses of AC, 11 cases of AML or MDS were identified, for an incidence of 0.32 cases per 1,000 patient years (95% Cl, 0.16 to 0.57) and a cumulative incidence at 5 years of 0.21% (95% Cl, 0.11 to 0.41%). In another analysis of 1,474 patients with breast cancer who received adjuvant treatment with doxorubicin-containing regimens in clinical trials conducted at University of Texas M.D. Anderson Cancer Center, the incidence was estimated at 1.5% at 10 years. In both experiences, patients who received regimens with higher cyclophosphamide dosages, who received radiotherapy, or who were aged 50 or older had an increased risk of secondary AML or MDS.

Pediatric patients are also at risk of developing secondary AML.

Effects at Site of Injection

Phlebosclerosis may result from an injection into a small vessel or from repeated injections into the same vein. Following the recommended administration procedures may minimize the risk of phlebitis/thrombophlebitis at the injection site (see DOSAGE AND ADMINISTRATION, Instruction for Use/Handling).

Extravasation

On intravenous administration of doxorubicin, extravasation may occur with or without an accompanying stinging or burning sensation, even if blood returns well on aspiration of the infusion needle. If any signs or symptoms of extravasation have occurred, the injection or infusion should be immediately terminated and restarted in another vein (see DOSAGE AND ADMINISTRATION).

Hepatic Impairment

Since metabolism and excretion of doxorubicin occurs predominantly by the hepatobiliary route, toxicity of recommended doses of doxorubicin can be enhanced by hepatic impairment; therefore, prior to individual dosing, evaluation of hepatic function is recommended using conventional laboratory tests such as SGOT, SGPT, alkaline phosphatase, and bilirubin (see DOSAGE AND ADMINISTRATION).

Immunosuppressant Effects/Increased Susceptibility to Infections

Administration of live or live attenuated vaccines in patients immunocompromised by chemotherapeutic agents including doxorubicin, may result in serious or fatal infections. Vaccination with a live vaccine should be avoided in patients receiving doxorubicin. Killed or inactivated vaccines may be administered; however, the response to such vaccines may be diminished.

Pregnancy Category D

Doxorubicin can cause fetal harm when administered to a pregnant woman. Doxorubicin was teratogenic and embryotoxic at doses of 0.8 mg/kg/day (about 1/13 the recommended human dose on a body surface area basis) when administered during the period of organogenesis in rats. Teratogenicity and embryotoxicity were also seen using discrete periods of treatment. The most susceptible was the 6- to 9-day gestation period at doses of 1.25 mg/kg/day and greater. Characteristic malformations included esophageal and intestinal atresia, tracheoesophageal fistula, hypoplasia of the urinary bladder and cardiovascular anomalies. Doxorubicin was embryotoxic (increase in embryofetal deaths) and abortifacient at 0.4 mg/kg/day (about 1/14 the recommended human dose on a body surface area basis) in rabbits when administered during the period of organogenesis.

There are no adequate and well-controlled studies in pregnant women. If doxorubicin is to be used during pregnancy, or if the patient becomes pregnant during therapy, the patient should be apprised of the potential hazard to the fetus. Women of childbearing age should be advised to avoid becoming pregnant.

PRECAUTIONS:

General

Doxorubicin is not an anti-microbial agent. Doxorubicin is emetigenic. Antiemetics may reduce nausea and vomiting; prophylactic use of antiemetics should be considered before administration of doxorubicin, particularly when given in conjunction with other emetigenic drugs. Doxorubicin should not be administered in combination with other cardiotoxic agents unless the patient's cardiac function is closely monitored. Patients receiving doxorubicin after stopping treatment with other cardiotoxic agents, especially those with long half-lives such as trastuzumab, may also be at an increased risk of developing cardiotoxicity. Physicians should avoid doxorubicin-based therapy for up to 24 weeks after stopping trastuzumab when possible. If doxorubicin used before this time, careful monitoring of cardiac function is recommended (see WARNINGS, DOSAGE AND ADMINISTRATION).

Information for Patients

Patients should be informed of the expected adverse effects of doxorubicin, including gastrointestinal symptoms (nausea, vomiting, diarrhea, and stomatitis) and potential neutropenic complications. Patients should consult their physician if vomiting, dehydration, fever, evidence of infection, symptoms of CHF, or injection-site pain occurs following therapy with doxorubicin. Patients should be informed that they will almost certainly develop alopecia. Patients should be advised that their urine may appear red for 1 to 2 days after administration of doxorubicin and that they should not be alarmed. Patients should understand that there is a risk of irreversible myocardial damage associated with treatment with doxorubicin, as well as a risk of treatment-related leukemia. Because doxorubicin may induce chromosomal damage in sperm, men undergoing treatment with doxorubicin should use effective contraceptive methods. Women treated with doxorubicin may develop irreversible amenorrhea, or premature menopause.

Drug Interactions

Doxorubicin is extensively metabolized by the liver. Changes in hepatic function induced by concomitant therapies may affect doxorubicin metabolism, pharmacokinetics, therapeutic efficacy, and/or toxicity. Toxicities associated with doxorubicin, especially hematologic and gastrointestinal events, may be increased when doxorubicin is used in combination with other cytotoxic drugs.

Paclitaxel

There have been a number of reports in the literature that describe an increase in cardiotoxicity when doxorubicin is co-administered with paclitaxel. Two published studies report that initial administration of paclitaxel infused over 24 hours followed by doxorubicin administered over 48 hours resulted in a significant decrease in doxorubicin clearance with more profound neutropenic and stomatitis episodes than the reverse sequence of administration.

Progesterone

In a published study, progesterone was given intravenously to patients with advanced malignancies (ECOG PS< 2) at high doses (up to 10 g over 24 hours) concomitantly with a fixed doxorubicin dose (60 mg/m^2) via bolus injection. Enhanced doxorubicin-induced neutropenia and thrombocytopenia were observed.

Verapamil

A study of the effects of verapamil on the acute toxicity of doxorubicin in mice revealed higher initial peak concentrations of doxorubicin in the heart with a higher incidence and severity of degenerative changes in cardiac tissue resulting in a shorter survival.

Cyclosporine

The addition of cyclosporine to doxorubicin may result in increases in AUC for both doxorubicin and doxorubicinol possibly due to a decrease in clearance of parent drug and a decrease in metabolism of doxorubicinol. Literature reports suggest that adding cyclosporine to doxorubicin results in more profound and prolonged hematologic toxicity than doxorubicin alone. Coma and/or seizures have also been described.

Dexrazoxane

In a clinical study of women with metastatic breast cancer, the concurrent use of the cardioprotectant, dexrazoxane, with the initiation of a regimen of fluorouracil, doxorubicin, and cyclophosphamide (FAC) was associated with a lower tumor response rate. Later initiation of dexrazoxane (after administration of a cumulative doxorubicin dose of 300 mg/m^2 of doxorubicin had been given as a component of FAC) was not associated with a reduction in chemotherapy activity. Dexrazoxane is only indicated for use in women with metastatic breast cancer who have received a cumulative doxorubicin dose of 300 mg/m^2 and are continuing with doxorubicin therapy.

Cytarabine

Necrotizing colitis manifested by typhlitis (cecal inflammation), bloody stools and severe and sometimes fatal infections have been associated with a combination of doxorubicin given by intravenous push daily for 3 days and cytarabine given by continuous infusion daily for 7 or more days.

Sorafenib

In clinical studies, both an increase of 21% and 47% and no change in the AUC of doxorubicin were observed with concomitant treatment with sorafenib 400 mg twice daily. The clinical significance of these findings is unknown.
Cyclophosphamide

The addition of cyclophosphamide to doxorubicin treatment does not affect exposure to doxorubicin, but may result in an increase in exposure to doxorubicinol, a metabolite. Doxorubicinol only has 5% of the cytotoxic activity of doxorubicin. Concurrent treatment with doxorubicin has been reported to exacerbate cyclophosphamide-induced hemorrhagic cystitis. Acute myeloid leukemia has been reported as a second malignancy after treatment with doxorubicin and cyclophosphamide.

Literature reports have also described the following drug interactions

Phenobarbital increases the elimination of doxorubicin; phenytoin levels may be decreased by doxorubicin; streptozocin (Zanosar®) may inhibit hepatic metabolism of doxorubicin; saquinavir in combination with cyclophosphamide, doxorubicin, and etoposide increased mucosal toxicity in patients with HIV-associated non-Hodgkin's lymphoma; and administration of live vaccines to immunosuppressed patients including those undergoing cytotoxic chemotherapy may be hazardous (see WARNINGS).

Laboratory Tests

Initial treatment with doxorubicin requires observation of the patient and periodic monitoring of complete blood counts, hepatic function tests, and left ventricular ejection fraction (see WARNINGS). Abnormalities of hepatic function tests may occur. Like other cytotoxic drugs, doxorubicin may induce "tumor-lysis syndrome" and hyperuricemia in patients with rapidly growing tumors. Blood uric acid levels, potassium, calcium, phosphate, and creatinine should be evaluated after initial treatment. Hydration, urine alkalinization, and prophylaxis with allopurinol to prevent hyperuricemia may minimize potential complications of tumor-lysis syndrome.

Carcinogenesis, Mutagenesis, Impairment of Fertility

Carcinogenicity studies have not been conducted with doxorubicin. Secondary acute myelogenous leukemia (AML) or myelodysplastic syndrome (MDS) have been reported in patients treated with doxorubicin-containing combination chemotherapy regimens (see WARNINGS). Pediatric patients treated with doxorubicin or other topoisomerase II inhibitors are at risk for developing acute myelogenous leukemia and other neoplasms. Doxorubicin was mutagenic in the in vitro Ames assay, and clastogenic in multiple in vitro assays (CHO cell, V79 hamster cell, human lymphoblast, and SCE assays) and the in vivo mouse micronucleus assay.

Doxorubicin decreased fertility in female rats at the doses of 0.05 and 0.2 mg/kg/day (about 1/200 and 1/50 the recommended human dose on a body surface area basis) when administered from 14 days before mating through late gestation period. A single IV dose of doxorubicin at 0.1 mg/kg (about 1/100 the recommended human dose on a body surface area basis) was toxic to male reproductive organs producing testicular atrophy and oligospermia in rats. Doxorubicin is mutagenic as it induced DNA damage in rabbit spermatozoa and dominant lethal mutations in mice. Therefore, doxorubicin may potentially induce chromosomal damage in human spermatozoa. Oligospermia or azoospermia were evidenced in men treated with doxorubicin, mainly in combination therapies. Men undergoing doxorubicin treatment should use effective contraceptive methods.

Doxorubicin was toxic to male reproductive organs in animal studies, producing testicular atrophy, diffuse degeneration of the seminiferous tubules, and hypospermia. Doxorubicin is mutagenic as it induces DNA damage in rabbit spermatozoa and dominant lethal mutations in mice. Therefore, doxorubicin can potentially induce chromosomal damage in human spermatozoa. Oligospermia or azoospermia were evidenced in men treated with doxorubicin, mainly in combination therapies. This effect may be permanent. However, sperm counts have been reported to return to normal levels in some instances. This may occur several years after the end of the therapy. Men undergoing doxorubicin treatment should use effective contraceptive methods.

In women, doxorubicin may cause infertility during the time of drug administration. Doxorubicin may cause amenorrhea. Ovulation and menstruation may return after termination of therapy, although premature menopause can occur. Recovery of menses is related to age at treatment.

Secondary acute myelogenous leukemia (AML) or myelodysplastic syndrome (MDS) have been reported in patients treated with anthracycline-containing adjuvant combination chemotherapy regimens (see WARNINGS, Hematologic Toxicity).

Pregnancy

Teratogenic Effects: Pregnancy Category D

(See WARNINGS).

Nursing Mothers

Doxorubicin and its major metabolite, doxorubicinol have been detected in the milk of at least one lactating patient (see CLINICAL PHARMACOLOGY, Pharmacokinetics). Because of the potential for serious adverse reactions in nursing infants from doxorubicin, mothers should be advised to discontinue nursing during doxorubicin therapy.

Pediatric Use

Pediatric patients are at increased risk for developing delayed cardiotoxicity. Follow-up cardiac evaluations are recommended periodically to monitor for this delayed cardiotoxicity (see WARNINGS). Doxorubicin, as a component of intensive chemotherapy regimens administered to pediatric patients, may contribute to prepubertal growth failure. It may also contribute to gonadal impairment, which is usually temporary. Pediatric patients treated with doxorubicin or other topoisomerase II inhibitors are at a risk for developing acute myelogenous leukemia and other neoplasms. Pediatric patients receiving concomitant doxorubicin and actinomycin-D have manifested acute "recall" pneumonitis at variable times after local radiation therapy.

Geriatric Use

An estimated 4,600 patients who were 65 and over were included in the reported clinical experience of doxorubicin use for various indications. No overall differences in safety and effectiveness were observed between these patients and younger patients, but greater sensitivity of some older individuals cannot be ruled out. The decision to use doxorubicin in the treatment of older patients should be based upon a consideration of overall performance status and concurrent illnesses, in addition to age of the individual patient.

ADVERSE REACTIONS:

Dose limiting toxicities of therapy are myelosuppression and cardiotoxicity. Other reactions reported are:

Cardiotoxicity

(See WARNINGS).

Cutaneous

Reversible complete alopecia occurs in most cases. Hyperpigmentation of nailbeds and dermal creases, primarily in pediatric patients, and onycholysis have been reported in a few cases. Radiation recall reaction has occurred with doxorubicin administration. Rash, itching, or photosensitivity may occur.

Gastrointestinal

Acute nausea and vomiting occurs frequently and may be severe. This may be alleviated by antiemetic therapy. Mucositis (stomatitis and esophagitis) may occur within 5 to 10 days of beginning therapy, and most patients recover from this adverse event within another 5 to 10 days. The effect may be severe leading to ulceration and represents a site of origin for severe infections. The dosage regimen consisting of administration of doxorubicin on three successive days results in greater incidence and severity of mucositis. Ulceration and necrosis of the colon, especially the cecum, may occur leading to bleeding or severe infections which can be fatal. This reaction has been reported in patients with acute non-lymphocytic leukemia treated with a 3-day course of doxorubicin combined with cytarabine. Anorexia, abdominal pain, dehydration, diarrhea, and hyperpigmentation of the oral mucosa have been occasionally reported.

Hematologic

(See WARNINGS).

Hypersensitivity

Fever, chills and urticaria have been reported occasionally. Anaphylaxis may occur. A case of apparent cross sensitivity to lincomycin has been reported.

Neurological

Peripheral neurotoxicity in the form of local-regional sensory and/or motor disturbances have been reported in patients treated intra-arterially with doxorubicin, mostly in combination with cisplatin. Animal studies have demonstrated seizures and coma in rodents and dogs treated with intra-carotid doxorubicin. Seizures and coma have been reported in patients treated with doxorubicin in combination with cisplatin or vincristine.

Ocular

Conjunctivitis, keratitis, and lacrimation occur rarely.

Other

Malaise/asthenia have been reported.

Adverse Reactions in Patients with Early Breast Cancer Receiving Doxorubicin-Containing Adjuvant Therapy

Safety data were collected from approximately 2,300 women who participated in a randomized, open-label trial (NSABP B-15) evaluating the use of AC versus CMF in the treatment of early breast cancer involving axillary lymph nodes. In the safety analysis, the follow-up data from all patients receiving AC were combined (N=1,492 evaluable patients) and compared with data from patients receiving conventional CMF (i.e., oral cyclophosphamide; N=739 evaluable patients). The most relevant adverse events reported in this study are provided in Table 2.

Table 2. Relevant Adverse Events in Patients with Early Breast Cancer Involving Axillary Lymph Nodes

 | AC* | Conventional CMF
 | N=1,492 | N=739
Treatment administration
Mean number of cycles | 3.8 | 5.5
Total cycles | 5,676 | 4,068
Adverse events, % of patients
Leukopenia
Grade 3 (1,000 to 1,999 /mm^3) | 3.4 | 9.4
Grade 4 (<1000/mm^3) | 0.3 | 0.3
Thrombocytopenia
Grade 3 (25,000 to 49,999 /mm^3) | 0 | 0.3
Grade 4 (<25,000 /mm^3) | 0.1 | 0
Shock, sepsis | 1.5 | 0.9
Systemic infection | 2.4 | 1.2
Nausea and vomiting
Nausea only | 15.5 | 42.8
Vomiting ≤ 12 hours | 34.4 | 25.2
Vomiting >12 hours | 36.8 | 12
Intractable | 4.7 | 1.6
Alopecia | 92.4 | 71.4
Partial | 22.9 | 56.3
Complete | 69.5 | 15.1
Weight loss
5 to 10% | 6.2 | 5.7
>10% | 2.4 | 2.8
Weight gain
5 to 10% | 10.6 | 27.9
>10% | 3.8 | 14.3
Cardiac function
Asymptomatic | 0.2 | 0.1
Transient | 0.1 | 0
Symptomatic | 0.1 | 0
Treatment-related death | 0 | 0

*Includes pooled data from patients who received either AC alone for 4 cycles, or who were treated with AC for 4 cycles followed by 3 cycles of CMF

OVERDOSAGE:

Acute overdosage with doxorubicin enhances the toxic effects of mucositis, leukopenia and thrombocytopenia. Treatment of acute overdosage consists of treatment of the severely myelosuppressed patient with hospitalization, antimicrobials, platelet transfusions and symptomatic treatment of mucositis. Use of hemopoietic growth factor (G-CSF, GM-CSF) may be considered.

The 200 mg doxorubicin hydrochloride injection vial is packaged as a multiple dose vial and caution should be exercised to prevent inadvertent overdosage.

Cumulative dosage with doxorubicin increases the risk of cardiomyopathy and resultant congestive heart failure (see WARNINGS). Treatment consists of vigorous management of congestive heart failure with digitalis preparations, diuretics, and after-load reducers such as ACE inhibitors.

DOSAGE AND ADMINISTRATION:

When possible, to reduce the risk of developing cardiotoxicity in patients receiving doxorubicin after stopping treatment with other cardiotoxic agents, especially those with long half-lives such as trastuzumab, doxorubicin-based therapy should be delayed until the other agents have cleared from the circulation (see WARNINGSand PRECAUTIONS, General).

Care in the administration of doxorubicin will reduce the chance of perivenous infiltration (see WARNINGS). It may also decrease the chance of local reactions such as urticaria and erythematous streaking. On intravenous administration of doxorubicin, extravasation may occur with or without an accompanying burning or stinging sensation, even if blood returns well on aspiration of the infusion needle. If any signs or symptoms of extravasation have occurred, the injection or infusion should be immediately terminated and restarted in another vein. If extravasation is suspected, intermittent application of ice to the site for 15 min. q.i.d. x 3 days may be useful. The benefit of local administration of drugs has not been clearly established. Because of the progressive nature of extravasation reactions, close observation and plastic surgery consultation is recommended. Blistering, ulceration and/or persistent pain are indications for wide excision surgery, followed by split-thickness skin grafting.

The most commonly used dose schedule when used as a single agent is 60 to 75 mg/m^2 as a single intravenous injection administered at 21-day intervals. The lower dosage should be given to patients with inadequate marrow reserves due to old age, or prior therapy, or neoplastic marrow infiltration.

Doxorubicin has been used concurrently with other approved chemotherapeutic agents. Evidence is available that in some types of neoplastic disease, combination chemotherapy is superior to single agents. The benefits and risks of such therapy continue to be elucidated. When used in combination with other chemotherapy drugs, the most commonly used dosage of doxorubicin is 40 to 60 mg/m^2 given as a single intravenous injection every 21 to 28 days.

In a large randomized study (NSABP B-15) of patients with early breast cancer involving axillary lymph nodes (see CLINICAL PHARMACOLOGY, CLINICAL STUDIES and ADVERSE REACTIONS, Adverse Reactions in Patients with Early Breast Cancer Receiving Doxorubicin-Containing Adjuvant Therapy), the combination dosage regimen of AC (doxorubicin 60 mg/m^2 and cyclophosphamide 600 mg/m^2) was administered intravenously on day 1 of each 21-day treatment cycle. Four cycles of treatment were administered.

Dose Modifications

Patients in the NSABP B-15 study could have dose modifications of AC to 75% of the starting doses for neutropenic fever/infection. When necessary, the next cycle of treatment cycle was delayed until the absolute neutrophil count (ANC) was ≥ 1,000 cells/mm^3 and the platelet count was ≥ 100,000 cells/mm^3 and nonhematologic toxicities had resolved.

Doxorubicin dosage must be reduced in case of hyperbilirubinemia as follows:

Plasma bilirubin concentration (mg/dL) | Dosage reduction (%)
1.2 to 3 | 50
3.1 to 5 | 75

Reconstitution Directions

It is recommended that doxorubicin be slowly administered into the tubing of a freely running intravenous infusion of Sodium Chloride Injection, USP, or 5% Dextrose Injection, USP. The tubing should be attached to a Butterfly® needle inserted preferably into a large vein. If possible, avoid veins over joints or in extremities with compromised venous or lymphatic drainage. The rate of administration is dependent on the size of the vein and the dosage. However, the dose should be administered in not less than 3 to 5 minutes. Local erythematous streaking along the vein as well as facial flushing may be indicative of too rapid an administration. A burning or stinging sensation may be indicative of perivenous infiltration and, if this occurs, the infusion should be immediately terminated and restarted in another vein. Perivenous infiltration may occur painlessly.

Doxorubicin should not be mixed with heparin or fluorouracil since it has been reported that these drugs are incompatible to the extent that a precipitate may form. Contact with alkaline solutions should be avoided since this can lead to hydrolysis of doxorubicin. Until specific compatibility data are available, it is not recommended that doxorubicin be mixed with other drugs.

Parenteral drug products should be inspected visually for particulate matter and discoloration prior to administration, whenever solution and container permit.

Handling and Disposal

Procedures for proper handling and disposal of anti-cancer drugs should be considered. Several guidelines on this subject have been published.^1-4 There is no general agreement that all the procedures recommended in the guidelines are necessary or appropriate. However, given the toxic nature of this substance, the following protective recommendations are provided:

- Personnel should be trained in good technique for reconstitution and handling.
- Pregnant staff should be excluded from working with this drug.
- Personnel handling doxorubicin should wear protective clothing: goggles, gowns and disposable gloves and masks.
- A designated area should be defined for reconstitution (preferably under a laminar flow system). The work surface should be protected by disposable, plastic-backed, absorbent paper.
- All items used for reconstitution, administration or cleaning, including gloves, should be placed in high-risk waste-disposal bags for high-temperature incineration.
- Spillage or leakage should be treated with dilute sodium hypochlorite (1% available chlorine) solution, preferably by soaking, and then water.
- All cleaning materials should be disposed of as indicated previously.
- In case of skin contact, thoroughly wash the affected area with soap and water or sodium bicarbonate solution. However, do not abrade the skin by using a scrub brush.
- In case of contact with the eye(s), hold back the eyelid(s) and flush the affected eye(s) with copious amounts of water for at least 15 minutes. Then seek medical evaluation by a physician.
- Always wash hands after removing gloves.

Caregivers of pediatric patients receiving doxorubicin should be counseled to take precautions (such as wearing latex gloves) to prevent contact with the patient’s urine and other body fluids for at least 5 days after each treatment.

HOW SUPPLIED:

Doxorubicin Hydrochloride Injection, USP, 2 mg per mL, a sterile product which contains no preservatives, is available as follows:

Product No. | NDC No.
88305 | 63323-883-05 | Doxorubicin hydrochloride 10 mg in a 5 mL single dose flip-top vial, packaged individually.
88310 | 63323-883-10 | Doxorubicin hydrochloride 20 mg in a 10 mL single dose flip-top vial, packaged individually.
88330 | 63323-883-30 | Doxorubicin hydrochloride 50 mg in a 25 mL single dose flip-top vial, packaged individually.
100161 | 63323-101-61 | Doxorubicin hydrochloride 200 mg in a 100 mL multiple dose vial, packaged individually.

REFRIGERATE AT:2° to 8°C (36° to 46°F).

Protect from light (keep in outer carton). Preservative Free. Discard unused portion.

The container closure is not made with natural rubber latex.

REFERENCES:

1. NIOSH Alert: Preventing occupational exposures to antineoplastic and other hazardous drugs in healthcare settings. 2004. U.S. Department of Health and Human Services, Public Health Service, Centers for Disease Control and Prevention, National Institute for Occupational Safety and Health, DHHS (NIOSH) Publication No. 2004-165.
2. OSHA Technical Manual, TED 1-0.15A, Section VI: Chapter 2. Controlling Occupational Exposure to Hazardous Drugs. OSHA, 1999. http://osha.gov/dts/osta/otm/otm_vi/otm _vi_2.html
3. American Society of Health-System Pharmacists. ASHP guidelines on handling hazardous drugs. Am J Health-Syst Pharm. 2006; 63:1172-1193.
4. Polovich, M., White, J. M., & Kelleher, L.O. (eds.) 2005. Chemotherapy and biotherapy guidelines and recommendations for human practice (2nd. ed.) Pittsburgh, PA: Oncology Nursing Society.

The brand names mentioned in this document are the trademarks of their respective owners.

PATIENT INFORMATION

Doxorubicin
(dakse-RU-besen)
Hydrochloride Injection, USP

Read this Patient information before you start receiving doxorubicin and before each infusion. This information leaflet does not take the place of talking with your doctor about your medical condition or your treatment.

What is the most important information I should know about doxorubicin?

Doxorubicin may cause serious side effects including:

• Heart problems. Doxorubicin may cause heart problems that may lead to death. These problems can happen during your treatment or months to years after stopping treatment. In some cases heart problems are irreversible. Your chance of heart problems is higher if you:

• already have heart problems

• have a history of radiation therapy or are currently receiving radiation therapy to your chest

• have had treatment with certain other anti-cancer medicines

• take other medicines that can affect your heart

Tell your doctor if you get any of these symptoms of heart problems:

• shortness of breath

• cough

• swelling of your feet and ankles

• fast heartbeat

Your doctor should do tests to check your heart before, during, and after your treatment with doxorubicin.

• Secondary cancers. Some people who have received doxorubicin have developed acute myelogenous leukemia (AML) or myelodysplastic syndrome (MDS). Your chance of developing a secondary cancer is higher if you receive doxorubicin along with other anti-cancer medicines or with radiation therapy.

• Decreased blood cell counts. Doxorubicin can cause a severe decrease in neutrophils (a type of white blood cells important in fighting in bacterial infections), red blood cells (blood cells that carry oxygen to the tissues), and platelets (important for clotting and to control bleeding).Your doctor will check your blood cell count during your treatment with doxorubicin and after you have stopped your treatment.

What is doxorubicin?

Doxorubicin is a prescription anti-cancer medicine used to treat certain types of cancers. Doxorubicin may be used alone or along with other anti-cancer medicines.

Who should not receive doxorubicin?

Do not receive doxorubicin if:

• your blood cell counts are too low: platelets (which help your blood to clot), red blood cells (which help to carry iron and oxygen throughout your body), and white blood cells (which help to fight infection)

• you have a severe liver problem

• you have had a recent heart attack or have severe heart problems

• you have had previous treatment with doxorubicin or certain other anticancer medicines and received the maximum dose allowed

• you are allergic to certain other anti-cancer medicines, doxorubicin hydrochloride, or any other ingredient in Doxorubicin Hydrochloride Injection, USP. See the end of this leaflet for a complete list of ingredients in Doxorubicin Hydrochloride Injection, USP.

Talk to your doctor before receiving doxorubicin if you have any of the conditions listed above.

What should I tell my doctor before receiving doxorubicin?

Before you receive doxorubicin, tell your doctor if you:

• have heart problems

• have had radiation treatment or currently receiving radiation therapy

• are over the age of 50

• have liver problems

• plan to receive any vaccines. Talk to your doctor about which vaccines are safe for you to receive during your treatment with doxorubicin. See “What should I avoid while receiving doxorubicin?”

• have any other medical conditions

• are pregnant or plan to become pregnant. Doxorubicin can harm your unborn baby. Women who may become pregnant should use effective birth control (contraception). Talk to your doctor about the best way to prevent pregnancy while receiving doxorubicin.

• are breastfeeding or plan to breast feed. Doxorubicin can pass into your breast milk and harm your baby. You and your doctor should decide if you will receive doxorubicin or breastfeed. You should not do both.

Tell your doctor about all the medicines you take, including prescription and non-prescription medicines, vitamins, and herbal supplements. Doxorubicin can interact with other medicines. Do not start any new medicine before you talk with the doctor that prescribed doxorubicin.

Know the medicines you take. Keep a list to show your doctor and pharmacist each time you get a new medicine.

How will I receive doxorubicin?

• Your doctor will prescribe doxorubicin in an amount that is right for you.

• Doxorubicin will be given to you by intravenous (IV) infusion into your vein.

• Your doctor will do regular blood tests to check for side effects of doxorubicin.

• Before receiving doxorubicin you may receive other medicines to prevent or treat side effects.

• Caregivers of children receiving doxorubicin should take precautions (such as wearing latex gloves) to prevent contact with the patient’s urine and other body fluids for at least 5 days after each treatment.

What should I avoid while taking doxorubicin?

• Avoid receiving live vaccines during treatment with doxorubicin. Talk to your doctor to find out which vaccines are safe for you while receiving doxorubicin. See “What should I tell my doctor before receiving doxorubicin?”

What are the possible side effects of doxorubicin?

Doxorubicin can cause serious side effects including:

• See "What is the most important information I should know about doxorubicin?"

Infusion site reactions. Serious infusion site reactions can happen with doxorubicin. Symptoms of infusion reaction may include:

• pain at injection site

• skin redness or swelling

• burning or stinging

• open skin sores at injection site

Your doctor will watch you closely while you are receiving doxorubicin and after your infusion for signs of a reaction. You may experience these reactions immediately or within 2 hours of infusion.

Change in the color of your urine. You may have red colored urine for 1 to 2 days after your infusion of doxorubicin. This is normal. Tell your doctor if it does not stop in a few days, or if you see what looks like blood or blood clots in your urine.

Infection. Call your doctor right away if you get any of the following signs of infection:

• fever (temperature of 100.4 F or greater) chills or shivering

• cough that brings up mucus

• burning or pain with urination

Doxorubicin may cause lower sperm counts and sperm problems in men.

This could affect your ability to father a child and cause birth defects. Men should use effective birth control (contraception) while receiving doxorubicin. Do not have unprotected sexual contact with a female who could become pregnant. Tell your doctor if you do have unprotected sexual contact with a female who could become pregnant. Talk to your doctor if this is a concern for you.

Irreversible amenorrhea or early menopause. Your periods (menstrual cycle) may completely stop when you receive doxorubicin. Your periods may or may not return after you complete your treatment of doxorubicin.

The most common side effects of doxorubicin include:

• hair loss (alopecia). Your hair may re-grow after your treatment.

• darkening of your nails or separation of your nails from your nailbed

• nausea

• vomiting

• lack of appetite or increased thirst

• bruise or bleed more easily

• abnormal heart beat

• a secondary cancer may occur when doxorubicin is combined with other chemotherapy agents.

• mouth sores

• weight changes

• stomach (abdominal) pain

• diarrhea

• eye problems

• allergic reactions. Call your doctor right away if you have any of the following symptoms of an allergic reaction:

• rash

• flushed face

• fever

• hives

• dizziness or feel faint

• itching

• shortness of breath or trouble breathing

• swelling of your lips or tongue

Tell your doctor or nurse if you have any side effect that bothers you or that does not go away.

These are not all of the possible side effects of doxorubicin. For more information, ask your doctor or pharmacist.

Call your doctor for medical advice about side effects. You may report side effects to FDA at 1-800-FDA-1088.

General information about the safe and effective use of doxorubicin.

Medicines are sometimes prescribed for purposes other than those listed in a Patient Information leaflet.

This leaflet summarizes the most important information about doxorubicin. If you would like more information, talk with your doctor. You can ask your doctor or pharmacist for information about doxorubicin that is written for healthcare professionals.

For more information, call 1-800-551-7176.

What are the ingredients of Doxorubicin Hydrochloride Injection, USP?

Active ingredient: Doxorubicin hydrochloride

Inactive ingredient: sodium chloride 0.9%, water for injection, hydrochloric acid and/or sodium hydroxide.

This Patient Information has been approved by the U.S. Food and Drug Administration.

www.fresenius-kabi.us
45771E
Revised: August 2016

PACKAGE LABEL

PACKAGE LABEL - PRINCIPAL DISPLAY - Doxorubicin 5 mL Single Dose Vial Label

DOXOrubicin Hydrochloride Injection, USP

10 mg per 5 mL
(2 mg per mL)

For intravenous use only.
Preservative free.

5 mL Single Dose Vial Rx only

PACKAGE LABEL - PRINCIPAL DISPLAY - Doxorubicin 5 mL Single Dose Vial Carton Panel

DOXOrubicin Hydrochloride Injection, USP
10 mg per 5 mL
(2 mg per mL)

For intravenous use only.

Preservative free.
Rx only
5 mL
Single Dose Vial

PACKAGE LABEL - PRINCIPAL DISPLAY - Doxorubicin 100 mL Multiple Dose Vial Label

DOXOrubicin Hydrochloride Injection, USP

200 mg per 100 mL
(2 mg per mL)

For intravenous use only.

Preservative free.

100 mL
Multiple Dose Vial Rx only

PACKAGE LABEL - PRINCIPAL DISPLAY - Doxorubicin 100 mL Multiple Dose Vial Carton Panel

DOXOrubicin Hydrochloride Injection, USP

200 mg per 100 mL
(2 mg per mL)

For intravenous use only.
Preservative free.

Rx only
100 mL
Multiple Dose Vial